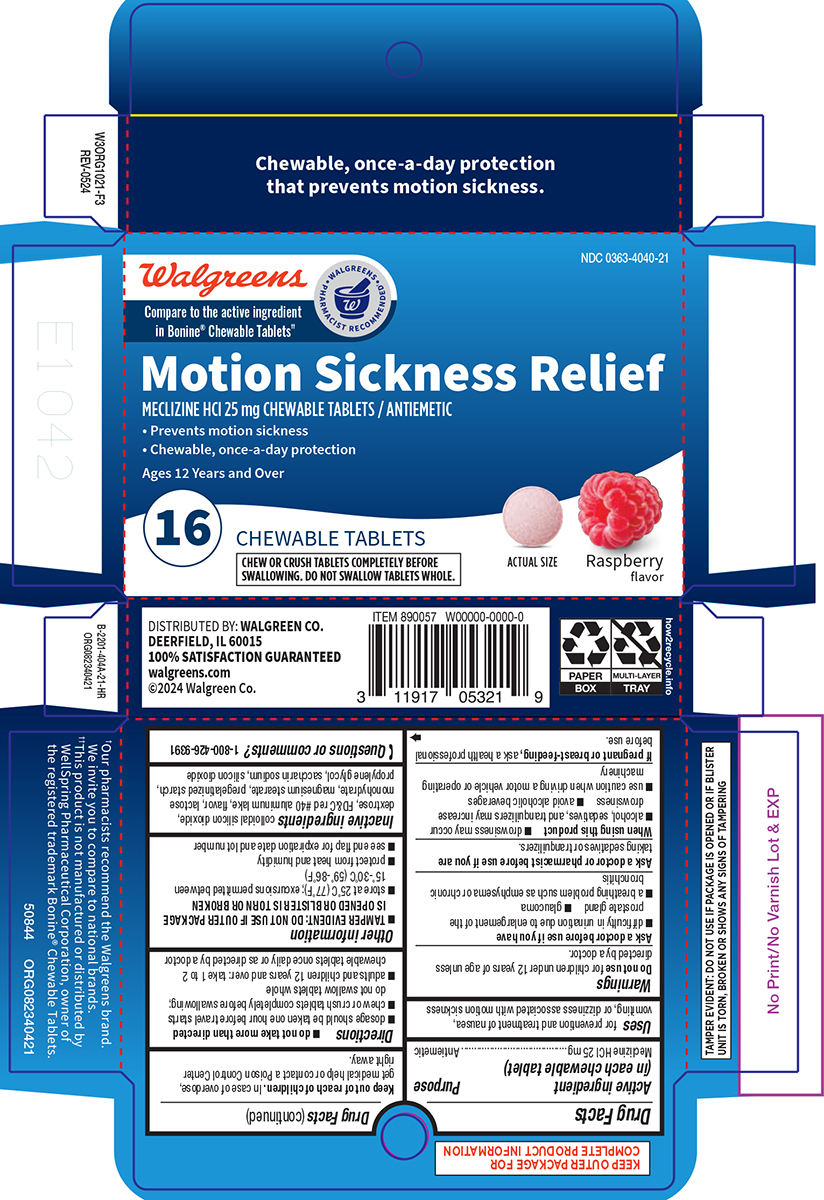 DRUG LABEL: Motion Sickness Relief
NDC: 0363-4040 | Form: TABLET, CHEWABLE
Manufacturer: Walgreen Company
Category: otc | Type: HUMAN OTC DRUG LABEL
Date: 20250520

ACTIVE INGREDIENTS: MECLIZINE HYDROCHLORIDE 25 mg/1 1
INACTIVE INGREDIENTS: SILICON DIOXIDE; DEXTROSE, UNSPECIFIED FORM; FD&C RED NO. 40 ALUMINUM LAKE; LACTOSE MONOHYDRATE; MAGNESIUM STEARATE; STARCH, CORN; PROPYLENE GLYCOL; SACCHARIN SODIUM

Walgreens 44-404A

Active ingredient (in each chewable tablet)

Meclizine HCl 25 mg

Purpose

Antiemetic

Uses

for prevention and treatment of nausea, vomiting, or dizziness associated with motion sickness

Warnings

Do not use

for children under 12 years of age unless directed by a doctor.

Ask a doctor before use if you have

- glaucoma
- difficulty in urination due to enlargement of the prostate gland
- a breathing problem such as emphysema or chronic bronchitis

Ask a doctor or pharmacist before use if you are

taking sedatives or tranquilizers.

When using this product

- drowsiness may occur
- alcohol, sedatives, and tranquilizers may increase drowsiness
- avoid alcoholic beverages
- use caution when driving a motor vehicle or operating machinery

If pregnant or breast-feeding,

ask a health professional before use.

Keep out of reach of children.

In case of overdose, get medical help or contact a Poison Control Center right away.

Directions

- do not take more than directed
- dosage should be taken one hour before travel starts
- chew or crush tablets completely before swallowing; do not swallow tablets whole
- adults and children 12 years and over: take 1 to 2 chewable tablets once daily or as directed by a doctor

Other information

- TAMPER EVIDENT: DO NOT USE IF OUTER PACKAGE IS OPENED OR BLISTER IS TORN OR BROKEN
- store at 25ºC (77ºF); excursions permitted between 15º-30ºC (59º-86ºF)
- protect from heat and humidity
- see end flap for expiration date and lot number

Inactive ingredients

colloidal silicon dioxide, dextrose, FD&C red #40 aluminum lake, flavor, lactose monohydrate, magnesium stearate, pregelatinized starch, propylene glycol, saccharin sodium, silicon dioxide

Questions or comments?

1-800-426-9391

Principal Display Panel

Walgreens
Compare to the active ingredient
in Bonine® Chewable Tablets††

• WALGREENS •
PHARMACIST RECOMMENDED

NDC 0363-4040-21

Motion Sickness Relief
MECLIZINE HCl 25 mg CHEWABLE TABLETS / ANTIEMETIC

• Prevents motion sickness
• Chewable, once-a-day protection
Ages 12 Years and Over

16

CHEWABLE TABLETS
CHEW OR CRUSH TABLETS COMPLETELY BEFORE
SWALLOWING. DO NOT SWALLOW TABLETS WHOLE.

ACTUAL SIZE
Raspberry
flavor

DISTRIBUTED BY: WALGREEN CO.
DEERFIELD, IL 60015
100% SATISFACTION GUARANTEED
walgreens.com
©2024 Walgreen Co.

TAMPER EVIDENT: DO NOT USE IF PACKAGE IS OPENED OR IF BLISTER
UNIT IS TORN, BROKEN OR SHOWS ANY SIGNS OF TAMPERING

†Our pharmacists recommend the Walgreens brand.
We invite you to compare to national brands.
††This product is not manufactured or distributed by
WellSpring Pharmaceutical Corporation, owner of
the registered trademark Bonine® Chewable Tablets.

50844 ORG082340421

Walgreens 44-404A